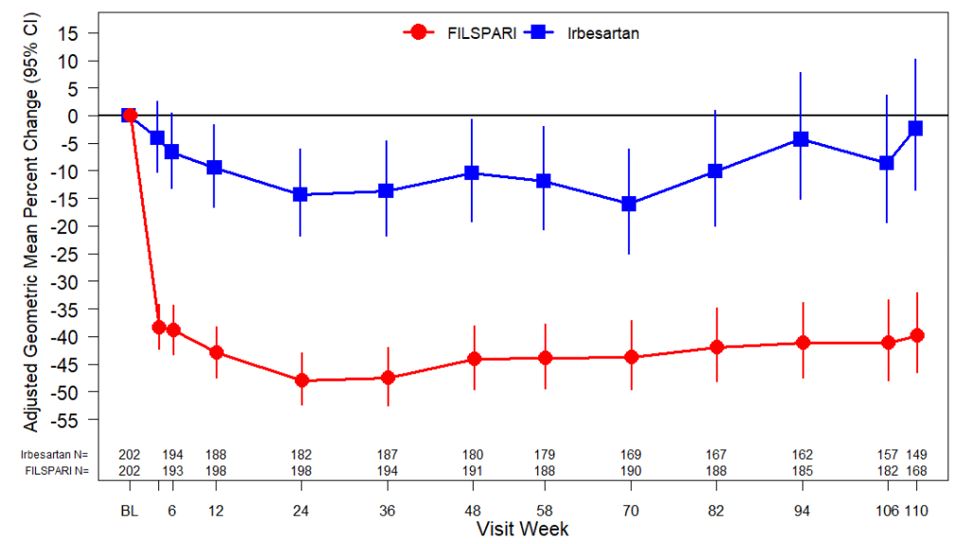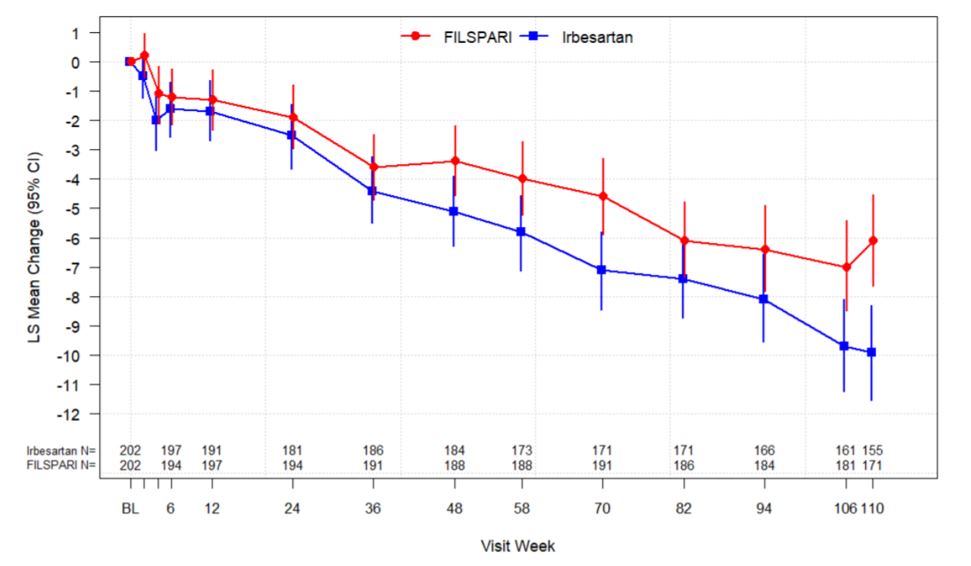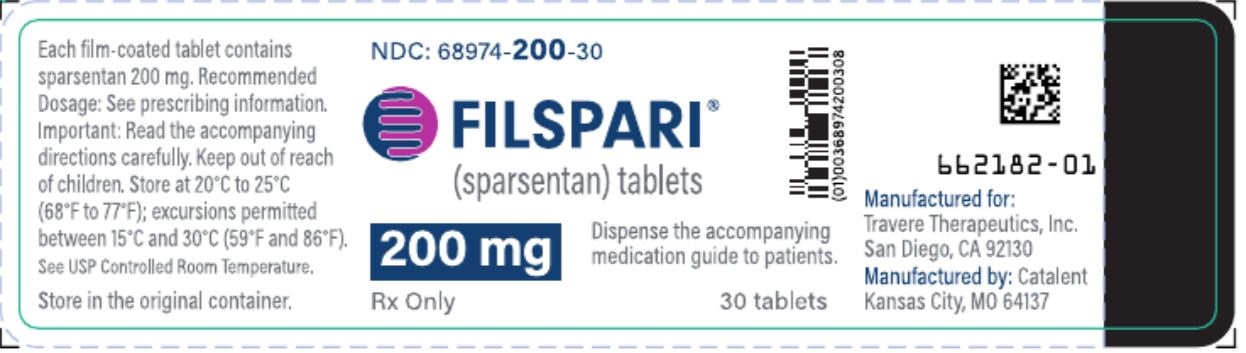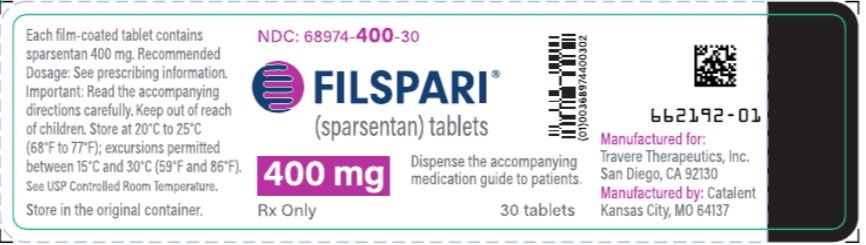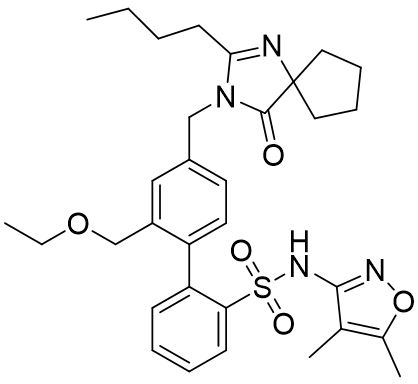 DRUG LABEL: FILSPARI
NDC: 68974-200 | Form: TABLET, FILM COATED
Manufacturer: Travere Therapeutics, Inc.
Category: prescription | Type: HUMAN PRESCRIPTION DRUG LABEL
Date: 20251217

ACTIVE INGREDIENTS: SPARSENTAN 200 mg/1 1
INACTIVE INGREDIENTS: ANHYDROUS LACTOSE; SODIUM STARCH GLYCOLATE TYPE A; SILICON DIOXIDE; MAGNESIUM STEARATE; MICROCRYSTALLINE CELLULOSE; POLYETHYLENE GLYCOL, UNSPECIFIED; POLYVINYL ALCOHOL, UNSPECIFIED; TALC; TITANIUM DIOXIDE

HIGHLIGHTS OF PRESCRIBING INFORMATION

These highlights do not include all the information needed to use FILSPARI® safely and effectively. See full prescribing information for FILSPARI®.
FILSPARI® (sparsentan) tablets, for oral use
Initial U.S. Approval: 2023

WARNING: HEPATOTOXICITY and EMBRYO-FETAL TOXICITY

See full prescribing information for complete boxed warning.

- FILSPARI is only available through a restricted distribution program called the FILSPARI Risk Evaluation and Mitigation Strategies (REMS) because of the risk of hepatotoxicity (5.2):
  - Some endothelin receptor antagonists have caused elevations of aminotransferases, hepatotoxicity, and liver failure (5.1).
  - Measure liver aminotransferases and total bilirubin prior to initiation of treatment and ALT and AST every 3 months during treatment (2.2, 2.6, 5.1).
  - Interrupt treatment and closely monitor patients developing aminotransferase elevations more than 3-times Upper Limit of Normal (ULN) (2.2, 2.6).
- Based on animal data, FILSPARI may cause fetal harm if used during pregnancy and is contraindicated in pregnancy (4, 5.3, 8.1).
  - For patients who can become pregnant, exclude pregnancy prior to the initiation of treatment with FILSPARI (2.3, 5.3, 8.3)
  - Use effective contraception prior to initiation of treatment, during treatment, and for two weeks after stopping FILSPARI (4, 5.3, 8.1, 8.3).
  - When pregnancy is detected, discontinue FILSPARI as soon as possible (5.3).

RECENT MAJOR CHANGES

- Boxed Warning | 8/2025
- Indications and Usage | 9/2024
- Dosage and Administration, Monitoring (2.2) | 8/2025
- Dosage and Administration, Pregnancy Testing (2.3) | 8/2025
- Warnings and Precautions, Hepatotoxicity (5) | 8/2025

1 INDICATIONS AND USAGE

FILSPARI is an endothelin and angiotensin II receptor antagonist indicated to slow kidney function decline in adults with primary immunoglobulin A nephropathy (IgAN) who are at risk for disease progression (1, 12.1).

2 DOSAGE AND ADMINISTRATION

- Prior to initiating treatment with FILSPARI, discontinue use of renin- angiotensin-aldosterone system (RAAS) inhibitors and endothelin receptor antagonists (ERAs) (2.1, 4, 7.1).
- Initiate treatment with FILSPARI at 200 mg orally once daily. After 14 days, increase to 400 mg once daily, as tolerated. When resuming FILSPARI after an interruption, consider re-titration (2.4).
- Instruct patients to swallow tablets whole with water prior to the morning or evening meal (2.5).

3 DOSAGE FORMS AND STRENGTHS

Tablets: 200 mg and 400 mg (3).

4 CONTRAINDICATIONS

- Pregnancy (4).
- Concomitant use with angiotensin receptor blockers (ARBs), ERAs, or aliskiren (4).

5 WARNINGS AND PRECAUTIONS

- Hypotension (5.4)
- Acute Kidney Injury (5.5)
- Hyperkalemia (5.6)
- Fluid Retention (5.7)

6 ADVERSE REACTIONS

Most common adverse reactions (≥5%) are hyperkalemia, hypotension (including orthostatic hypotension), peripheral edema, dizziness, anemia, and acute kidney injury (6.1).

To report SUSPECTED ADVERSE REACTIONS, contact Travere Therapeutics at 1-877-659-5518 or FDA at 1-800-FDA-1088 or www.fda.gov/medwatch.

7 DRUG INTERACTIONS

- Strong CYP3A inhibitors: Avoid concomitant use. Increased sparsentan exposure (2.7, 7.2, 12.3).
- Moderate CYP3A inhibitors: Monitor adverse reactions. Increased sparsentan exposure (7.2, 12.3).
- Strong CYP3A inducers: Avoid concomitant use. Decreased sparsentan exposure (7.3, 12.3).
- Antacids: Avoid use within 2 hours before or after use of sparsentan. May decrease exposure to sparsentan (7.4, 11).
- Acid reducing agents: Avoid concomitant use. May decrease exposure to sparsentan (7.4).
- Non-steroidal anti-inflammatory drugs (NSAIDs) including selective cyclooxygenase (COX-2) inhibitors: Monitor for signs of worsening renal function. Increased risk of kidney injury (7.5).
- CYP2B6, 2C9, and 2C19 substrates: Monitor for substrate efficacy. Decreased exposure of these substrates (7.6, 12.3).
- Sensitive P-gp and BCRP substrates: Avoid concomitant use. Increased exposure to substrates (7.7, 12.3).
- Agents Increasing Serum Potassium: Increased risk of hyperkalemia, monitor serum potassium frequently (5.6, 7.8).

8 USE IN SPECIFIC POPULATIONS

- Lactation: Advise not to breastfeed (8.2).

FULL PRESCRIBING INFORMATION

WARNING: HEPATOTOXICITY and EMBRYO-FETAL TOXICITY

Because of the risk of hepatotoxicity, FILSPARI is available only through a restricted program called the FILSPARI REMS. Under the FILSPARI REMS, prescribers, patients, and pharmacies must enroll in the program [see Warnings and Precautions (5.1, 5.2)].

Hepatotoxicity

Some Endothelin Receptor Antagonists (ERAs) have caused elevations of aminotransferases, hepatotoxicity, and liver failure. In clinical studies, elevations in aminotransferases (ALT or AST) of at least 3-times the Upper Limit of Normal (ULN) have been observed in up to 3.5% of FILSPARI-treated patients, including cases confirmed with rechallenge.

Measure transaminases and bilirubin before initiating treatment and then every 3 months during treatment. Interrupt treatment and closely monitor patients who develop aminotransferase elevations more than 3-times ULN [see Dosage and Administration (2.2, 2.6), Warnings and Precautions (5.1)].

FILSPARI should generally be avoided in patients with elevated aminotransferases (>3-times ULN) at baseline because monitoring for hepatotoxicity may be more difficult and these patients may be at increased risk for serious hepatotoxicity [see Dosage and Administration (2.2, 2.6), Warnings and Precautions (5.1)].

Embryo-Fetal Toxicity

FILSPARI is contraindicated for use during pregnancy because it may cause fetal harm if used by pregnant patients. Therefore, in patients who can become pregnant, exclude pregnancy prior to initiation of FILSPARI.
Advise use of effective contraception before the initiation of treatment, during treatment, and for two weeks after discontinuation of treatment with FILSPARI. When pregnancy is detected, discontinue FILSPARI as soon as possible [see Dosage and Administration (2.3), Contraindications (4), Warnings and Precautions (5.3), Use in Specific Populations (8.1, 8.3)].

1 INDICATIONS AND USAGE

FILSPARI is indicated to slow kidney function decline in adults with primary immunoglobulin A nephropathy (IgAN) who are at risk for disease progression.

2 DOSAGE AND ADMINISTRATION

2.1 General Considerations

Prior to initiating treatment with FILSPARI, discontinue use of renin-angiotensin-aldosterone system (RAAS) inhibitors and endothelin receptor antagonists (ERAs) [see Contraindications (4), Drug Interactions (7.1)].

2.2 Monitoring

Initiate treatment with FILSPARI only after measuring aminotransferase levels and total bilirubin. Avoid initiation in patients with elevated aminotransferases greater than 3 times ULN. Continue required monitoring every 3 months during treatment with FILSPARI [see Dosage and Administration (2.6), Warnings and Precautions (5.1)].

2.3 Pregnancy Testing

Exclude pregnancy before initiating treatment with FILSPARI [see Warnings and Precautions (5.3), Use in Specific Populations (8.1, 8.3)].

2.4 Recommended Dosage

Initiate treatment with FILSPARI at 200 mg orally once daily. After 14 days, increase to the recommended dose of 400 mg once daily, as tolerated. When resuming treatment with FILSPARI after an interruption, consider titration of FILSPARI, starting at 200 mg once daily. After 14 days, increase to the recommended dose of 400 mg once daily [see Drug Interactions (7.2)].

2.5 Administration

- Instruct patient to swallow tablets whole with water prior to the morning or evening meal.
- Maintain the same dosing pattern in relationship to meals.
- If a dose is missed, take the next dose at the regularly scheduled time. Do not take double or extra doses.

2.6 Dosage Adjustment for Aminotransferase Elevations

If aminotransferase levels increase, adjust monitoring and treatment plan according to Table 1.

Do not resume treatment in patients who have experienced clinical symptoms of hepatotoxicity or in patients whose hepatic enzyme levels and bilirubin have not returned to pretreatment levels.

Table 1: Dosage Adjustment and Monitoring in Patients Developing Aminotransferase Elevations Greater Than 3 Times ULN
ALT/AST levels | Treatment and monitoring recommendations
Greater than 3 times and less than or equal to 8 times ULN | Confirm elevation with a repeat measure.; If confirmed, interrupt treatment, and monitor aminotransferase levels and bilirubin at least weekly, and INR as needed, until the levels return to pretreatment values and the patient is asymptomatic.; Do not resume treatment if any of the following occurs without other cause found:; - ALT or AST greater than 3 times ULN and total bilirubin greater than 2 times ULN or INR greater than 1.5 - ALT or AST greater than 3 times ULN, with symptoms of fatigue, nausea, vomiting, right upper quadrant pain or tenderness, fever, rash, and/or eosinophilia (greater than 5% eosinophils) - ALT or AST greater than 5 times ULN for more than 2 weeks; If treatment is resumed, initiate FILSPARI at 200 mg once daily, with reassessment of hepatic enzyme levels and bilirubin within 3 days. Close monitoring is required in these patients [see Dosage and Administration (2.2, 2.4)].
Greater than 8 times ULN | Stop treatment permanently if no other cause found.
ALT = alanine aminotransferase; AST = aspartate aminotransferase; INR = international normalized ratio; ULN = upper limit of normal.

2.7 Dosage Modification for Concomitant Use with Strong CYP3A Inhibitors

Avoid concomitant use of strong CYP3A inhibitors with FILSPARI.

If a strong CYP3A inhibitor cannot be avoided, interrupt treatment with FILSPARI [see Drug Interactions (7.2)].

3 DOSAGE FORMS AND STRENGTHS

FILSPARI is supplied as film-coated, modified oval, white to off-white tablets debossed on one side and plain on the other in the following strengths:

200 mg debossed with “105”
400 mg debossed with “021”

4 CONTRAINDICATIONS

Use of FILSPARI is contraindicated in patients who are pregnant [see Dosage and Administration (2.3), Warnings and Precautions (5.3), Use in Specific Populations (8.1)].

Do not coadminister FILSPARI with ARBs, ERAs, or aliskiren [see Dosage and Administration (2.1), Drug Interactions (7.1)].

5 WARNINGS AND PRECAUTIONS

5.1 Hepatotoxicity

Elevations in ALT or AST of at least 3-fold ULN have been observed in up to 3.5% of FILSPARI-treated patients, including cases confirmed with rechallenge [see Adverse Reactions (6.1)]. While no concurrent elevations in bilirubin greater than 2-times ULN or cases of liver failure were observed in FILSPARI-treated patients in clinical trials, some endothelin receptor antagonists have caused elevations of aminotransferases, hepatotoxicity, and liver failure. To reduce the risk of potential serious hepatotoxicity, measure serum aminotransferase levels and total bilirubin prior to initiation of treatment and then every 3 months during treatment [See Dosage and Administration (2.2)].

Advise patients with symptoms suggesting hepatotoxicity (nausea, vomiting, right upper quadrant pain, fatigue, anorexia, jaundice, dark urine, fever, or itching) to immediately stop treatment with FILSPARI and seek medical attention. If aminotransferase levels are abnormal at any time during treatment, interrupt FILSPARI and monitor as recommended [see Dosage and Administration (2.6)].

Consider re-initiation of FILSPARI only when hepatic enzyme levels and bilirubin return to pretreatment values and only in patients who have not experienced clinical symptoms of hepatotoxicity [see Dosage and Administration (2.2, 2.6)].

Avoid initiation of FILSPARI in patients with elevated aminotransferases (greater than 3-times ULN) because monitoring hepatotoxicity in these patients may be more difficult and these patients may be at increased risk for serious hepatotoxicity [see Dosage and Administration (2.2, 2.6), and Warnings and Precautions (5.2)].

5.2 FILSPARI REMS

For all patients, FILSPARI is available only through a restricted program under a REMS called the FILSPARI REMS because of the risk of hepatotoxicity [see Warnings and Precautions (5.1)].

Important requirements of the FILSPARI REMS include the following:

- Prescribers must be certified with the FILSPARI REMS by enrolling and completing training.
- All patients must enroll in the FILSPARI REMS prior to initiating treatment and comply with monitoring requirements [see Dosage and Administration (2.2, 2.6), Warnings and Precautions (5.1)].
- Pharmacies that dispense FILSPARI must be certified with the FILSPARI REMS and must dispense only to patients who are authorized to receive FILSPARI.

Further information is available at www.filsparirems.com or 1-833-513-1325.

5.3 Embryo-Fetal Toxicity

Based on data from animal reproduction studies, FILSPARI may cause fetal harm when administered to a pregnant patient and is contraindicated for use during pregnancy. The available human data for endothelin receptor antagonists do not establish the presence or absence of fetal harm related to the use of FILSPARI. Counsel patients who can become pregnant of the potential risk to a fetus. Exclude pregnancy before initiating treatment with FILSPARI. Advise patients who can become pregnant to use effective contraception prior to initiation of treatment, during treatment, and for two weeks after discontinuation of treatment with FILSPARI. When pregnancy is detected, discontinue FILSPARI as soon as possible [see Dosage and Administration (2.3), Contraindications (4), Use in Specific Populations (8.1, 8.3)].

5.4 Hypotension

Hypotension has been observed in patients treated with ARBs and endothelin receptor antagonists (ERAs) and was observed in clinical studies with FILSPARI. In the PROTECT trial, there was a greater incidence of hypotension-associated adverse events, some serious, including dizziness, in patients treated with FILSPARI compared to irbesartan [see Adverse Reactions (6.1)].

In patients at risk for hypotension, consider eliminating or adjusting other antihypertensive medications and maintaining appropriate volume status.

If hypotension develops, despite elimination or reduction of other antihypertensive medications, consider a dose reduction or dose interruption of FILSPARI. A transient hypotensive response is not a contraindication to further dosing of FILSPARI, which can be given once blood pressure has stabilized.

5.5 Acute Kidney Injury

Monitor kidney function periodically. Drugs that inhibit the renin-angiotensin system can cause acute kidney injury. Patients whose kidney function may depend in part on the activity of the renin-angiotensin system (e.g., patients with renal artery stenosis, chronic kidney disease, severe congestive heart failure, or volume depletion) may be at particular risk of developing acute kidney injury on FILSPARI. Consider withholding or discontinuing therapy in patients who develop a clinically significant decrease in kidney function while on FILSPARI.

5.6 Hyperkalemia

Monitor serum potassium periodically and treat appropriately. Patients with advanced kidney disease or taking concomitant potassium-increasing drugs (e.g., potassium supplements, potassium-sparing diuretics), or using potassium-containing salt substitutes are at increased risk for developing hyperkalemia. Dosage reduction or discontinuation of FILSPARI may be required [see Dosage and Administration (2.4), Adverse Reactions (6.1)].

5.7 Fluid Retention

Fluid retention may occur with endothelin receptor antagonists and has been observed in clinical studies with FILSPARI [see Adverse Reactions (6.1)]. FILSPARI has not been evaluated in patients with heart failure.

If clinically significant fluid retention develops, evaluate the patient to determine the cause and the potential need to initiate or modify the dose of diuretic treatment then consider modifying the dose of FILSPARI.

6 ADVERSE REACTIONS

Clinically significant adverse reactions that appear in other sections of the label include:

- Hepatotoxicity [see Warnings and Precautions (5.1)]
- Embryo-Fetal Toxicity [see Warnings and Precautions (5.3)]
- Hypotension [see Warnings and Precautions (5.4)]
- Acute Kidney Injury [see Warnings and Precautions (5.5)]
- Hyperkalemia [see Warnings and Precautions (5.6)]
- Fluid Retention [see Warnings and Precautions (5.7)]

6.1 Clinical Trials Experience

Because clinical trials are conducted under widely varying conditions, adverse reaction rates observed in the clinical trials of a drug cannot be directly compared to rates in the clinical trials of another drug and may not reflect the rates observed in practice.

The safety of FILSPARI was evaluated in PROTECT (NCT03762850), a randomized, double-blind, active-controlled clinical study in adults with IgAN.

The data below reflect FILSPARI exposure in 202 patients with a median duration of 110 weeks.

The most common adverse reactions are presented in Table 2.

Table 2: Adverse Reactions Reported in 2% or More of Subjects Treated with FILSPARI
 | FILSPARI (N = 202) n (%) | Irbesartan (N = 202) n (%)
Hyperkalemia^1 | 34 (17) | 27 (13)
Hypotension (including orthostatic hypotension) | 33 (16) | 13 (6)
Peripheral edema^1 | 33 (16) | 29 (14)
Dizziness^1 | 32 (16) | 14 (7)
Anemia | 16 (8) | 9 (4)
Acute kidney injury | 12 (6) | 5 (2)
Transaminase elevations^2 | 7 (3.5) | 8 (4.0)
^1 Includes related terms.
^2 Elevations in ALT or AST greater than 3-fold ULN.

Laboratory Tests

Initiation of FILSPARI may cause an initial small decrease in estimated glomerular filtration rate (eGFR) that occurs within the first 4 weeks of starting therapy and then stabilizes.

The incidence of a hemoglobin decrease >2 g/dL compared to baseline and below the lower limit of normal was greater for the FILSPARI arm (19%) compared to the irbesartan arm (13%). This decrease is thought to be in part due to hemodilution. There were no treatment discontinuations due to anemia or hemoglobin decrease in the PROTECT study.

7 DRUG INTERACTIONS

7.1 Renin-Angiotensin System Inhibitors and ERAs

Do not coadminister FILSPARI with ARBs, ERAs, or aliskiren [see Dosage and Administration (2.1), Contraindications (4)].

Combined use of these agents is associated with increased risks of hypotension, syncope, hyperkalemia, and changes in renal function (including acute renal failure).

7.2 Strong and Moderate CYP3A Inhibitors

Avoid concomitant use of FILSPARI with strong CYP3A inhibitors. If a strong CYP3A inhibitor cannot be avoided, interrupt treatment with FILSPARI. When resuming treatment with FILSPARI, consider dose titration [see Dosage and Administration (2.4, 2.7), Clinical Pharmacology (12.3)].

Monitor blood pressure, serum potassium, edema, and kidney function regularly when used concomitantly with moderate CYP3A inhibitors [see Warnings and Precautions (5.4, 5.5, 5.6, 5.7)]. No FILSPARI dose adjustment is needed.

Sparsentan is a CYP3A substrate. Concomitant use with a strong CYP3A inhibitor increases sparsentan Cmax and AUC [see Clinical Pharmacology (12.3)], which may increase the risk of FILSPARI adverse reactions.

7.3 Strong CYP3A Inducers

Avoid concomitant use with a strong CYP3A inducer. Sparsentan is a CYP3A substrate. Concomitant use with a strong CYP3A inducer decreases sparsentan Cmax and AUC [see Clinical Pharmacology (12.3)], which may reduce FILSPARI efficacy.

7.4 Antacids and Acid Reducing Agents

Administer FILSPARI 2 hours before or after administration of antacids. Avoid concomitant use of acid reducing agents (histamine H2 receptor antagonist and PPI proton pump inhibitor) with FILSPARI. Sparsentan exhibits pH-dependent solubility [see Description (11)]. Antacids or acid reducing agents may decrease sparsentan exposure which may reduce FILSPARI efficacy.

7.5 Non-Steroidal Anti-Inflammatory Agents (NSAIDs), Including Selective Cyclooxygenase-2 (COX-2) Inhibitors

Monitor for signs of worsening renal function with concomitant use with NSAIDs (including selective COX-2 inhibitors). In patients with volume depletion (including those on diuretic therapy) or with impaired kidney function, concomitant use of NSAIDs (including selective COX-2 inhibitors) with drugs that antagonize the angiotensin II receptor may result in deterioration of kidney function, including possible kidney failure [see Warnings and Precautions (5.5)]. These effects are usually reversible.

7.6 CYP2B6, 2C9, and 2C19 Substrates

Monitor for efficacy of the concurrently administered CYP2B6, 2C9, and 2C19 substrates and consider dosage adjustment in accordance with the Prescribing Information. Sparsentan is an inducer of CYP2B6, 2C9, and 2C19. Sparsentan decreases exposure of these substrates [see Clinical Pharmacology (12.3)], which may reduce efficacy related to these substrates.

7.7 P-gp and BCRP Substrates

Avoid concomitant use of sensitive substrates of P-gp and BCRP with FILSPARI. Sparsentan is an inhibitor of P-gp and BCRP. Sparsentan may increase exposure of these transporter substrates [see Clinical Pharmacology (12.3)], which may increase the risk of adverse reactions related to these substrates.

7.8 Agents Increasing Serum Potassium

Monitor serum potassium frequently in patients treated with FILSPARI and other agents that increase serum potassium. Concomitant use of FILSPARI with potassium-sparing diuretics, potassium supplements, potassium-containing salt substitutes, or other drugs that raise serum potassium levels may result in hyperkalemia [see Warnings and Precautions (5.6)].

8 USE IN SPECIFIC POPULATIONS

8.1 Pregnancy

Risk Summary

Based on data from animal reproductive toxicity studies, FILSPARI may cause fetal harm, including birth defects and fetal death, when administered to a pregnant patient and is contraindicated during pregnancy [see Contraindications (4)]. Available data from reports of pregnancy in clinical trials with FILSPARI are insufficient to identify a drug-associated risk of major birth defects, miscarriage, or other adverse maternal or fetal outcomes. Available data from postmarketing reports and published literature over decades of use with ERA in the same class as FILSPARI have not identified an increased risk of fetal harm; however, these data are limited. Methodological limitations of these postmarketing reports and published literature include lack of a control group; limited information regarding dose, duration, and timing of drug exposure; and missing data. These limitations preclude establishing a reliable estimate of the risk of adverse fetal and neonatal outcomes with maternal ERA use. In animal reproduction studies, oral administration of sparsentan to pregnant rats throughout organogenesis at 10-times the maximum recommended human dose (MRHD) in mg/day caused teratogenic effects in rats, including craniofacial malformations, skeletal abnormalities, increased embryo-fetal lethality, and reduced fetal weights (see Data). Advise pregnant patients of the potential risk to the fetus.

The background risk of major birth defects and miscarriage for the indicated population is unknown. All pregnancies have a background risk of birth defect, loss, or other adverse outcomes. In the U.S. general population, the estimated background risk of major birth defects and miscarriage in clinically recognized pregnancies is 2-4% and 15-20%, respectively.

Data

Animal Data

In embryo-fetal development studies in pregnant rats and rabbits, teratogenicity and/or developmental toxicity were observed, which were attributed to the antagonism of endothelin type A (ETA) and angiotensin II type 1 (AT1) receptors.

In pregnant rats, oral administration of sparsentan throughout organogenesis at doses of 80, 160, and 240 mg/kg/day resulted in dose-dependent teratogenic effects in the form of craniofacial malformations, skeletal abnormalities, increased embryo-fetal lethality, and reduced fetal weights at all doses tested. The area under the curve (AUC) at the lowest dose tested (80 mg/kg/day) was approximately 10 times the AUC at the MRHD of 400 mg/day. In pregnant rabbits, oral administration of sparsentan throughout organogenesis at doses of 2.5, 10 and 40 mg/kg/day resulted in maternal death and abortions at 10 and 40 mg/kg/day which provided exposures approximately 0.1 times and 0.2 times the AUC at the MRHD, respectively. An increase in a fetal variation (supernumerary cervical ribs) occurred at the high dose of 40 mg/kg/day.

In the pre- and postnatal development study in rats, oral administration of sparsentan during pregnancy and the lactational period at doses of 5, 20, or 80 mg/kg/day resulted in maternal death, body weight loss/reduced body weight gain, and adverse clinical signs at 80 mg/kg/day. An increase in pup deaths occurred at 80 mg/kg/day (approximately 10 times the AUC at MRHD) during the neonatal period through weaning, and decreased growth occurred at ≥ 20 mg/kg/day (approximately 2.6 times the AUC at the MRHD) after weaning. The NOAEL for pre- and postnatal development in rats was 5 mg/kg/day, approximately 0.7 times the AUC at the MRHD.

8.2 Lactation

Risk Summary

There are no data on the presence of sparsentan in human milk, the effects on the breastfed infant, or the effect on milk production. Because of the potential for adverse reactions, such as hypotension in breastfed infants, advise patients not to breastfeed during treatment with FILSPARI.

8.3 Females and Males of Reproductive Potential

Based on data from animal reproductive toxicity studies, FILSPARI may cause fetal harm, including birth defects and fetal death, when administered to a pregnant patient and is contraindicated during pregnancy [see Contraindications (4), Use in Specific Populations (8.1)].

Pregnancy Testing
Exclude pregnancy before initiating FILSPARI in females of reproductive potential. The patient should contact their physician immediately for pregnancy testing if onset of menses is delayed or pregnancy is suspected. If the pregnancy test is positive, the physician and patient should discuss the risks to their pregnancy and the fetus.

Contraception
Patients who can become pregnant who are using FILSPARI must use an effective method of contraception prior to initiation of treatment, during treatment, and for two weeks after discontinuation of treatment with FILSPARI to prevent pregnancy [see Warnings and Precautions (5.3)].

8.4 Pediatric Use

The safety and efficacy of FILSPARI in pediatric patients have not been established.

8.5 Geriatric Use

Of the total number of subjects in the PROTECT study of FILSPARI, 15 (7.4%) were 65 and older. No overall differences in safety or effectiveness were observed between these subjects and younger subjects.

8.6 Hepatic Impairment

Avoid use of FILSPARI in patients with any hepatic impairment (Child-Pugh class A-C) because of the potential risk of serious liver injury [see Warnings and Precautions (5.1), Clinical Pharmacology (12.3)].

10 OVERDOSAGE

There is no experience with overdose with FILSPARI. Sparsentan has been given in doses up to 1600 mg/day in healthy volunteers, or up to 400 mg/day in IgAN patients. Overdose of FILSPARI may result in decreased blood pressure. In the event of an overdose, standard supportive measures should be taken, as required. Dialysis is unlikely to be effective because sparsentan is highly protein-bound.

11 DESCRIPTION

FILSPARI (sparsentan) is an endothelin and angiotensin II receptor antagonist. The chemical name of sparsentan is 2-[4-[(2-butyl-4-oxo-1,3-diazaspiro[4.4]non-1-en-3-yl)methyl]-2-(ethoxymethyl)phenyl]-N-(4,5-dimethyl-1,2-oxazol-3-yl)benzenesulfonamide.

Sparsentan is a white to off-white powder, which is practically insoluble in water. Sparsentan has pH-dependent solubility, with intrinsic solubility of 1.48 and 0.055 mg/mL under pH 1.2 and 6.8, respectively. Sparsentan has a molecular weight of 592.76 g/mol, a molecular formula of C32H40N4O5S, and the following structure:

FILSPARI is available as film-coated 200 mg and 400 mg strength immediate release tablets for oral administration.

The inactive ingredients in FILSPARI are colloidal silicon dioxide, lactose anhydrous, magnesium stearate, silicified microcrystalline cellulose, and sodium starch glycolate. Film-coating is composed of macrogol/polyethylene glycol, polyvinyl alcohol-partially hydrolyzed, talc, and titanium dioxide.

12 CLINICAL PHARMACOLOGY

12.1 Mechanism of Action

Sparsentan is a single molecule with antagonism of the endothelin type A receptor (ETAR) and the angiotensin II type 1 receptor (AT1R). Sparsentan has high affinity for both the ETAR (Ki= 12.8 nM) and the AT1R (Ki=0.36 nM), and greater than 500-fold selectivity for these receptors over the endothelin type B and angiotensin II subtype 2 receptors. Endothelin 1 and angiotensin II are thought to contribute to the pathogenesis of IgAN via the ETAR and AT1R, respectively.

12.2 Pharmacodynamics

Dose-response information is not available. At the recommended dose regimen, no statistically significant exposure-response (E-R) relationship was identified between sparsentan exposure and the percentage reduction from baseline in UPCR at Week 36 over the observed sparsentan exposure range. No clinically meaningful E-R relationships were observed for hypotension of any grade and peripheral edema worst grade. A statistically significant relationship was observed between sparsentan exposures and the incidence of hyperkalemia of any grade.

Cardiac Electrophysiology

In a randomized, positive-, and placebo-controlled study in healthy subjects, sparsentan caused QTcF prolongation with maximal mean effect of 8.8 msec (90% CI: 5.9, 11.8) at 800 mg and 8.1 msec (90% CI: 5.2, 11.0) at 1600 mg. The underlying mechanism behind the observed QTc prolongation is unknown but is unlikely to be mediated via direct inhibition of hERG channels. At the recommended dose, no clinically relevant QTc prolongation (i.e., >20 msec) is expected.

12.3 Pharmacokinetics

The pharmacokinetics of sparsentan are presented as geometric mean (% coefficient of variation) unless otherwise specified. The Cmax and AUC of sparsentan increase less than proportionally following administration of single doses of 200 mg to 1600 mg. Sparsentan showed time-dependent pharmacokinetics which may be related to the drug inducing its own metabolism over time. Steady-state plasma levels are reached within 7 days with no accumulation of exposure at the approved recommended dosage. Following a single oral dose of 400 mg sparsentan, the mean Cmax and AUC are 7.0 μg/mL and 83.0 μg×h/mL, respectively. Following daily doses of 400 mg sparsentan, the steady-state mean Cmax and AUC are 6.5 μg/mL and 63.6 μg×h/mL, respectively.

Absorption

Following a single oral dose of 400 mg sparsentan, the median (minimum to maximum) time to peak plasma concentration is approximately 3 hours (2 to 8 hours).

Effect of Food

Sparsentan AUC and Cmax increased by 22% and 108%, respectively, following administration of a single oral 800 mg dose with a high fat, high calorie meal (1000 kcal, 50% fat) [see Dosage and Administration (2.5)]. No clinically significant differences in sparsentan pharmacokinetics were observed following administration of a single 200 mg dose with a high fat, high calorie meal.

Distribution

The apparent volume of distribution at steady state is 61.4 L at the approved recommended dosage.

Sparsentan is >99% bound to human plasma proteins.

Elimination

The clearance of sparsentan is time-dependent which may be related to the drug inducing its own metabolism over time. The apparent clearance (CL/F) of sparsentan is 3.88 L/h following the initial 400 mg dose then increases to 5.11 L/h at steady state.

The half-life of sparsentan is estimated to be 9.6 hours at steady state.

Metabolism

Cytochrome P450 3A is the major isozyme responsible for the metabolism of sparsentan.

Excretion

After a single dose of radiolabeled sparsentan 400 mg to healthy subjects, approximately 80% of the dose was recovered in feces (9% unchanged) and 2% in urine (negligible amount unchanged). 82% of the dosed radioactivity was recovered within a 10-day collection period.

Specific Populations

No clinically significant differences in the pharmacokinetics of sparsentan were observed based on age (18 – 73 years), sex, race, mild to moderate renal impairment (eGFR 30 to 89 mL/min/1.73 m^2), or mild to moderate hepatic impairment (Child-Pugh class A or B). Patients with severe hepatic impairment (Child-Pugh class C) and eGFR <30 mL/min/1.73 m^2 have not been studied.

Drug Interaction Studies

Clinical Studies and Model-Informed Approaches

Effect of Other Drugs on Sparsentan

Strong CYP3A inhibitors: Concomitant use with itraconazole (strong CYP3A inhibitor) increased sparsentan Cmax by 25% and AUC by 174%.

Moderate CYP3A inhibitors: Concomitant use with cyclosporine (moderate CYP3A inhibitor) increased sparsentan Cmax by 41% and AUC by 70%.

Strong CYP3A inducers: Coadministration of rifampin (strong CYP3A inducer) is predicted to decrease sparsentan Cmax by 23% and AUC0-inf by 47% at steady state.

Effect of Sparsentan on Other Drugs

No clinically significant differences in the pharmacokinetics of midazolam (sensitive CYP3A4 substrate) or pitavastatin (OATP1B1, OATP1B3, P-gp, and BCRP substrate) were observed when co-administered with sparsentan. In addition, sparsentan had no clinically significant effect on serum creatinine levels (an endogenous biomarker of OAT2, OCT2, MATE1, and MATE2K) or on 6β-hydroxycortisol (an endogenous biomarker of OAT3).

CYP2B6 substrates: Concomitant use with sparsentan decreased the exposure of bupropion (CYP2B6 substrate) Cmax by 32% and AUC by 33%.

In Vitro Studies

CYP Enzymes: Sparsentan is a substrate of CYP3A. Sparsentan is both an inhibitor and inducer of CYP3A and an inducer of CYP2B6, CYP2C9, and CYP2C19.

Transporters: Sparsentan is a substrate of P-gp and BCRP but is not a substrate of OATP1B1 or OATP1B3. Sparsentan is an inhibitor of P-gp, BCRP, OATP1B3, and OAT3 but does not inhibit MRP, OATP1B1, NTCP, OCT2, OAT1, MATE1, or MATE2K at relevant concentrations.

13 NONCLINICAL TOXICOLOGY

13.1 Carcinogenesis, Mutagenesis, and Impairment of Fertility

Carcinogenesis: In the two-year rat carcinogenicity study, there was no evidence of increased incidence of neoplasia in male rats orally administered at 15 mg/kg/day (the only dose evaluated) and in female rats orally administered up to 240 mg/kg/day, which provided an exposure approximately 0.7 times and 26 times the AUC at the MRHD, respectively. In the 26-week transgenic mouse study, there was no evidence of increased incidence of neoplasia in male and female mice orally administered sparsentan at doses up to 600 mg/kg/day.

Mutagenesis: There was no evidence of mutagenicity or clastogenicity for sparsentan in in vitro bacteria reverse mutation and chromosomal aberration assays, or in an in vivo rat micronucleus study.

Impairment of fertility: In a fertility and early embryonic development study in rats, oral administration of sparsentan at doses of 20, 80, and 320 mg/kg/day for at least 36 (females) and 49 (males) days did not result in any adverse effects on estrous cycles, mating, fertility, sperm evaluation, or pregnancy incidence at doses up to 320 mg/kg/day, which provided approximately 10 and 14 times the AUC at the MRHD for males and females, respectively. Male reproductive organ toxicity was not evident in chronic toxicity studies with sparsentan at exposures up to 10 times and 1.3 times the AUC at the MRHD in rats and monkeys, respectively.

14 CLINICAL STUDIES

The effect of FILSPARI on proteinuria and kidney function (estimated glomerular filtration rate, eGFR) was assessed in a randomized, double-blind, active-controlled, multicenter, global study (PROTECT, NCT03762850) in adults with biopsy-proven primary IgAN, eGFR ≥30 mL/min/1.73 m^2, and total urine protein ≥1.0 g/day on a stable dose of maximally-tolerated RAS inhibitor treatment. Patients with chronic kidney disease due to another condition in addition to IgAN or those who had been recently treated with systemic immunosuppressants were excluded.

Patients were randomized (1:1) to either FILSPARI (400 mg once daily following 200 mg once daily for 14 days) or irbesartan (300 mg once daily following 150 mg once daily for 14 days). Rescue immunosuppressive treatment could be initiated per investigator discretion during the trial. Concomitant use of sodium-glucose cotransporter-2 (SGLT2) inhibitors, other RAS inhibitors, and aldosterone blockers were prohibited.

The primary efficacy endpoint for the interim analysis was the change from baseline in urine protein/creatinine ratio (UPCR) at Week 36 based on the first 281 randomized patients who had reached the Week 36 visit. The key secondary efficacy endpoint for the final analysis was the rate of change in eGFR over a 110-week period following initiation of randomized therapy.

The 404 patients who enrolled and received study medication had a mean age of 46 years (range 18 to 76 years); 70% were male, 67% White, 28% Asian, and 1% Black or African American. Approximately 78% had a history of hypertension, 11% had diabetes or impaired fasting glucose, and 56% had hematuria based on urine dipstick. At baseline, the mean eGFR was 57 mL/min/1.73 m^2, the geometric mean UPCR was 1.2 g/g, and 49 (12%) patients had proteinuria >3.5 g/24 hours.

Urine Protein/Creatinine Ratio (UPCR)

The trial met the prespecified primary endpoint of relative change from baseline in UPCR at Week 36 based on an interim analysis of 281 randomized patients who had reached the Week 36 visit. The interim analysis showed a 45% decrease in UPCR at Week 36 relative to baseline for patients treated with FILSPARI compared to a 15% decrease for patients treated with irbesartan resulting in a 35% reduction in the ratio of mean UPCR (95% CI: 23% to 45% reduction; p<0.0001). In the final analysis of 404 randomized patients, the treatment effects in UPCR observed at Week 36 and Week 110 were consistent with the results obtained at the interim analysis. The mean percent change from baseline over the course of the double-blind period is displayed in Figure 1.

Figure 1: Geometric Mean Percent Change from Baseline in Urine Protein-to-Creatinine Ratio by Visit through Week 110 (PROTECT, FAS)

Adjusted GMPC of UPCR was based on MMRM stratified by screening eGFR and total urine protein excretion. MMRM analysis includes UPCR data during the double-blind period up to Week 110 regardless of treatment discontinuation or immunosuppressive therapy initiation. Missing data were imputed using multiple imputation under assumptions of missing at random and missing not at random depending on the patient’s intercurrent event status. Baseline was defined as the last non-missing observation on or prior to the start of dosing. Counts in axis table represent number of subjects with observed UPCR data by visit and treatment group. BL=baseline; CI=confidence interval; FAS=full analysis set; GMPC=geometric mean percent change; LS=least squares; MMRM=mixed-model repeated measures; N= number of subjects with available data at the time of analysis; UPCR=urine protein/creatinine ratio.

Estimated Glomerular Filtration Rate (eGFR)

In the final analysis of 404 randomized patients, FILSPARI reduced the rate of decline in kidney function from baseline to Week 110 compared to irbesartan. The mean eGFR slope from baseline to Week 110 was -3.0 mL/min/1.73 m^2 per year for FILSPARI and -4.2 mL/min/1.73 m^2 per year for irbesartan, corresponding to a treatment effect of 1.2 mL/min/1.73 m^2 per year (95 %CI: 0.2 to 2.1; p=0.0168). The mean change from baseline in eGFR during the double-blind period is shown in Figure 2. The treatment effect on the rate of change in eGFR through Week 110 was generally consistent across key subgroups, including key demographic (such as age, sex, race, ethnicity, and region) and baseline disease (such as baseline BMI and baseline proteinuria) characteristics. The treatment benefit with FILSPARI on the rate of change in eGFR through Week 110 was not evident in patients with an eGFR ≥90 mL/min/1.73 m^2; however, there was a small number of patients in this subgroup.

Figure 2: Absolute Change in eGFR (mL/min/1.73 m^2) by Visit (FAS)

*eGFR was calculated using the CKD-EPI equation. Baseline was defined as the last non-missing observation on or prior to the start of dosing. The analysis includes eGFR data during the double-blind period up to Week 110 regardless of treatment discontinuation or immunosuppressive therapy initiation. Rescue immunosuppressive treatment for IgAN was initiated in 7 (3%) and 18 (9%) patients in the FILSPARI and irbesartan group respectively. BL=baseline; CI=confidence interval; CKD-EPI=Chronic Kidney Disease Epidemiology Collaboration; eGFR=estimated glomerular filtration rate; FAS=full analysis set; IgAN=immunoglobulin A nephropathy; LS=least squares; N=number of subjects with available data at the time of analysis.

16 HOW SUPPLIED/STORAGE AND HANDLING

FILSPARI is supplied in bottles of 30 film-coated tablets.

- 200 mg tablets are film-coated, modified oval, white to off-white, debossed with “105” on one side and plain on the other side, available in bottles of 30 tablets with child-resistant caps (NDC 68974-200-30).
- 400 mg tablets are film-coated, modified oval, white to off-white, debossed with “021” on one side and plain on the other side, available in bottles of 30 tablets with child-resistant caps (NDC 68974-400-30).

Storage

Store at 20°C to 25°C (68°F to 77°F), excursions permitted to 15°C to 30°C (59°F to 86°F). Store FILSPARI in its original container.

17 PATIENT COUNSELING INFORMATION

Advise patients to read the FDA-approved patient labeling (Medication Guide).

Restricted access

Advise the patient that FILSPARI is only available through a restricted access program called the FILSPARI REMS because of the risk of hepatotoxicity, and that FILSPARI is available only from certified pharmacies that are enrolled in the FILSPARI REMS.

As a component of the FILSPARI REMS, prescribers must review the contents of the FILSPARI Medication Guide with the patient before initiating FILSPARI and patients must sign the FILSPARI REMS Patient Enrollment Form to confirm that they understand the risks of FILSPARI.

Instruct patients of the risk of hepatotoxicity associated with FILSPARI.

Hepatotoxicity

Advise patients with symptoms suggesting hepatotoxicity (nausea, vomiting, right upper quadrant pain, fatigue, anorexia, jaundice, dark urine, fever, or itching) to immediately stop taking FILSPARI and seek medical attention [see Dosage and Administration (2.2, 2.4, 2.6), Warnings and Precautions (5.1)].

Discuss with the patient the requirement to measure serum aminotransferases every 3 months [see Dosage and Administration (2.2, 2.6), Warnings and Precautions (5.1, 5.2)].

Embryo-Fetal Toxicity

Counsel patients who can become pregnant about the need to use effective methods of contraception prior to treatment with FILSPARI, during treatment, and for two weeks after treatment discontinuation. Patients who can become pregnant should have a negative pregnancy test prior to initiation of treatment with FILSPARI [see Dosage and Administration (2.3), Contraindications (4), Warnings and Precautions (5.3), Use in Specific Populations (8.1, 8.3)].

Patients should be instructed to immediately contact their physician if they suspect they may be pregnant. Patients should seek additional contraceptive advice from a gynecologist or similar expert as needed.

Educate and counsel patients who can become pregnant on the use of emergency contraception in the event of unprotected sex or contraceptive failure.

Lactation

Advise patients not to breastfeed during treatment with FILSPARI [see Use in Specific Populations (8.2)].

Drug Interactions

Advise patients to inform their healthcare provider of all concomitant medications, including prescription medications, over-the-counter drugs, vitamins/supplements, herbal products, and grapefruit [see Contraindications (4), Warnings and Precautions (5.4, 5.5, 5.6, 5.7), Drug Interactions (7)].

Other Risks Associated with FILSPARI

Inform patients of other risks associated with FILSPARI, including:

- Hypotension: Advise patients to remain hydrated [see Warnings and Precautions (5.4)].
- Hyperkalemia: Advise patients not to use potassium supplements or salt substitutes that contain potassium without consulting their healthcare provider [see Warnings and Precautions (5.6)].

Dosing

Advise patients to take the full daily dose with water prior to the morning or evening meal. Maintain the same dosing pattern in relationship to meals. If a dose is missed, take the next dose at the regularly scheduled time. Do not take double or extra doses [see Dosage and Administration (2.5)].
Distributed by Travere Therapeutics, Inc., San Diego, CA 92130

FILSPARI is a registered trademark of Travere Therapeutics, Inc.

Medication Guide
FILSPARI® (fil spah ree)
(sparsentan)
tablets

What is the most important information I should know about FILSPARI?

FILSPARI can cause serious side effects, including:

- Liver problems.
  - FILSPARI can cause changes in liver tests. Liver failure was not observed in people treated with FILSPARI in clinical studies, but some medicines that are like FILSPARI can cause liver failure. Your healthcare provider will do blood tests to check your liver before starting treatment with FILSPARI and then every 3 months during treatment. Your healthcare provider may temporarily stop or permanently stop treatment with FILSPARI if you have changes in your liver tests.
    Stop taking FILSPARI and get medical help right away if you develop any of the following signs of liver problems during treatment with FILSPARI:

- nausea or vomiting
- pain on the upper right side of your stomach area
- tiredness
- loss of appetite

- yellowing of your skin or the white part of your eyes (jaundice)
- dark “tea-colored” urine
- fever
- itching

Because of the risk for liver problems, FILSPARI is only available through a restricted access program called the FILSPARI Risk Evaluation and Mitigation Strategy (REMS). Before you begin treatment with FILSPARI, your healthcare prescriber will explain the FILSPARI REMS program, you must read, and agree to all of the requirements of the FILSPARI REMS.
2. Serious birth defects
  FILSPARI can cause serious birth defects if taken during pregnancy.
  - Patients who can become pregnant should not be pregnant when they start taking FILSPARI or become pregnant during treatment with FILSPARI or for two weeks after stopping treatment with FILSPARI.
  - Patients who can become pregnant should have a negative pregnancy test before starting treatment with FILSPARI.
    Patients who can become pregnant are those who:
    - have entered puberty, even if they have not started their menstrual period, and
    - have a uterus, and
    - have not gone through menopause. Menopause means that you have not had a menstrual period for at least 12 months for natural reasons, or that you have had your ovaries removed.

Patients who cannot become pregnant are those who:

    - have not yet entered puberty, or
    - do not have a uterus, or
    - have gone through menopause. Menopause means that you have not had a menstrual period for at least 12 months for natural reasons, or that you have had your ovaries removed, or
    - are infertile for any other medical reason and this infertility is permanent and cannot be reversed.
  - Patients who can become pregnant should use effective birth control before starting treatment with FILSPARI, during treatment with FILSPARI, and for two weeks after stopping FILSPARI because the medicine may still be in your body.
    - Talk with your healthcare provider or gynecologist (a healthcare provider who specializes in reproduction) to find out about options for effective forms of birth control that you may use to prevent pregnancy during treatment with FILSPARI.
    - If you decide that you want to change the form of birth control that you use, talk with your healthcare provider or gynecologist to be sure that you choose another effective form of birth control.
  - Do not have unprotected sex. Talk to your healthcare provider or pharmacist right away if you have unprotected sex or if you think your birth control has failed. Your healthcare provider may talk with you about using emergency birth control.
  - Tell your healthcare provider right away if you miss a menstrual period or think you may be pregnant.

See “What are the possible side effects of FILSPARI?” for more information about side effects.

What is FILSPARI?

FILSPARI is a prescription medicine used to slow kidney function decline in adults with a kidney disease called primary immunoglobulin A nephropathy (IgAN), who are at risk for their disease getting worse.

It is not known if FILSPARI is safe and effective in children.

Who Should not take FILSPARI?

Do not take FILSPARI if you:

- are pregnant, plan to become pregnant, or become pregnant during treatment with FILSPARI. FILSPARI may cause serious birth defects. See “What is the most important information I should know about FILSPARI?”
- are taking an angiotensin receptor blocker, endothelin receptor antagonist, or aliskiren.

Ask your healthcare provider or pharmacist if you are not sure if you take one of these medicines.

Before taking FILSPARI, tell your healthcare provider about all of your medical conditions, including if you:

- have liver problems
- are pregnant or plan to become pregnant during treatment with FILSPARI. FILSPARI may cause serious birth defects. See “What is the most important information I should know about FILSPARI?”
- are breastfeeding or plan to breastfeed. It is not known if FILSPARI passes into your breast milk. Do not breastfeed during treatment with FILSPARI. Talk to your healthcare provider about the best way to feed your baby during treatment with FILSPARI.

Tell your healthcare provider about all the medicines you take, including prescription and over-the-counter medicines, vitamins, herbal supplements, and grapefruit. FILSPARI and other medicines may affect each other and cause side effects. Do not start any new medicine until you check with your healthcare provider.

Especially tell your healthcare provider if you take:

- nonsteroidal anti-inflammatory drugs (NSAIDs)
- potassium-containing medicines, potassium supplements, or salt substitutes containing potassium
- blood pressure medicines
- antacids, including histamine (H2) receptor blocker or proton pump inhibitor (PPI) medicines

Ask your healthcare provider or pharmacist if you are not sure if you take one of these medicines.

How should I take FILSPARI?

- FILSPARI will be provided to you by a certified pharmacy. Your healthcare provider will give you complete details.
- Take FILSPARI exactly as your healthcare provider tells you to take it. Do not stop taking FILSPARI unless your healthcare provider tells you.
- Your healthcare provider may change your dose, temporarily stop, or permanently stop treatment with FILSPARI if you develop side effects.
- Take FILSPARI whole with water before your morning or evening meal. Take your dose before the same meal each day.
- If you miss a dose, take the next dose at the regularly scheduled time. Do not take 2 doses at the same time or take extra doses.
- If you take an antacid, take FILSPARI 2 hours before or 2 hours after you take your antacid.
- If you take too much FILSPARI, call your healthcare provider or go to the nearest hospital emergency room right away.

What are the possible side effects of FILSPARI?

FILSPARI can cause serious side effects, including:

- Liver Problems. See “What is the most important information I should know about FILSPARI?”
- Serious birth defects. See “What is the most important information I should know about FILSPARI?”
- Low blood pressure. Low blood pressure is common during treatment with FILSPARI and can also be serious. Tell your healthcare provider if you feel dizzy, light-headed, or faint. Stay hydrated during treatment with FILSPARI.
- Worsening of kidney function. This is common during treatment with FILSPARI and can also be serious. Your healthcare provider will check your kidney function during treatment with FILSPARI.
- Increased potassium in your blood. This is common during treatment with FILSPARI and can also be serious. Your healthcare provider will check your potassium blood level during treatment with FILSPARI.
- Fluid retention. FILSPARI can cause your body to hold too much water. Tell your healthcare provider right away if you have any unusual weight gain or swelling of your ankles or legs.

The most common side effects of FILSPARI also include:

- swelling of hands, legs, ankles, and feet (peripheral edema)
- dizziness

- low red blood cells (anemia)

These are not all of the possible side effects of FILSPARI.

Call your doctor for medical advice about side effects. You may report side effects to FDA at 1-800-FDA-1088.

How should I store FILSPARI?

- Store FILSPARI at room temperature between 68°F to 77°F (20°C to 25°C).
- Store FILSPARI in the original container.
- The bottle has a child-resistant closure.

Keep FILSPARI and all medicines out of the reach of children.

General information about the safe and effective use of FILSPARI.

Medicines are sometimes prescribed for purposes other than those listed in the Medication Guide. Do not use FILSPARI for a condition for which it was not prescribed. Do not give FILSPARI to other people, even if they have the same symptoms that you have. It may harm them. You can ask your pharmacist or healthcare provider for information about FILSPARI that is written for health professionals.

What are the ingredients in FILSPARI?

Active ingredient: sparsentan

Inactive ingredients: colloidal silicon dioxide, lactose anhydrous, magnesium stearate, silicified microcrystalline cellulose, and sodium starch glycolate. Tablets are film coated with material containing macrogol/polyethylene glycol, polyvinyl alcohol-partially hydrolyzed, talc, and titanium dioxide.

Distributed by Travere Therapeutics, Inc., San Diego, CA 92130
FILSPARI is a registered trademark of Travere Therapeutics, Inc.
For more information, go to www.FILSPARI.com or call 1-877-659-5518.

This Medication Guide has been approved by the U.S. Food and Drug Administration.

Revised: August 2025

PRINCIPAL DISPLAY PANEL - 200 mg Tablet Bottle Label

NDC 68974-200-30
30 Tablets

FILSPARI®
(sparsentan) tablets

200 mg

Rx Only

Manufactured for:
Travere Therapeutics, Inc.,
San Diego, CA 92130

Manufactured by:
Catalent
Kansas City, MO 64137

PRINCIPAL DISPLAY PANEL - 400 mg Tablet Label

NDC 68974-400-30
30 Tablets

FILSPARI®
(sparsentan) tablets

400 mg

Rx Only

Manufactured for:
Travere Therapeutics, Inc.,
San Diego, CA 92130

Manufactured by:
Catalent
Kansas City, MO 64137